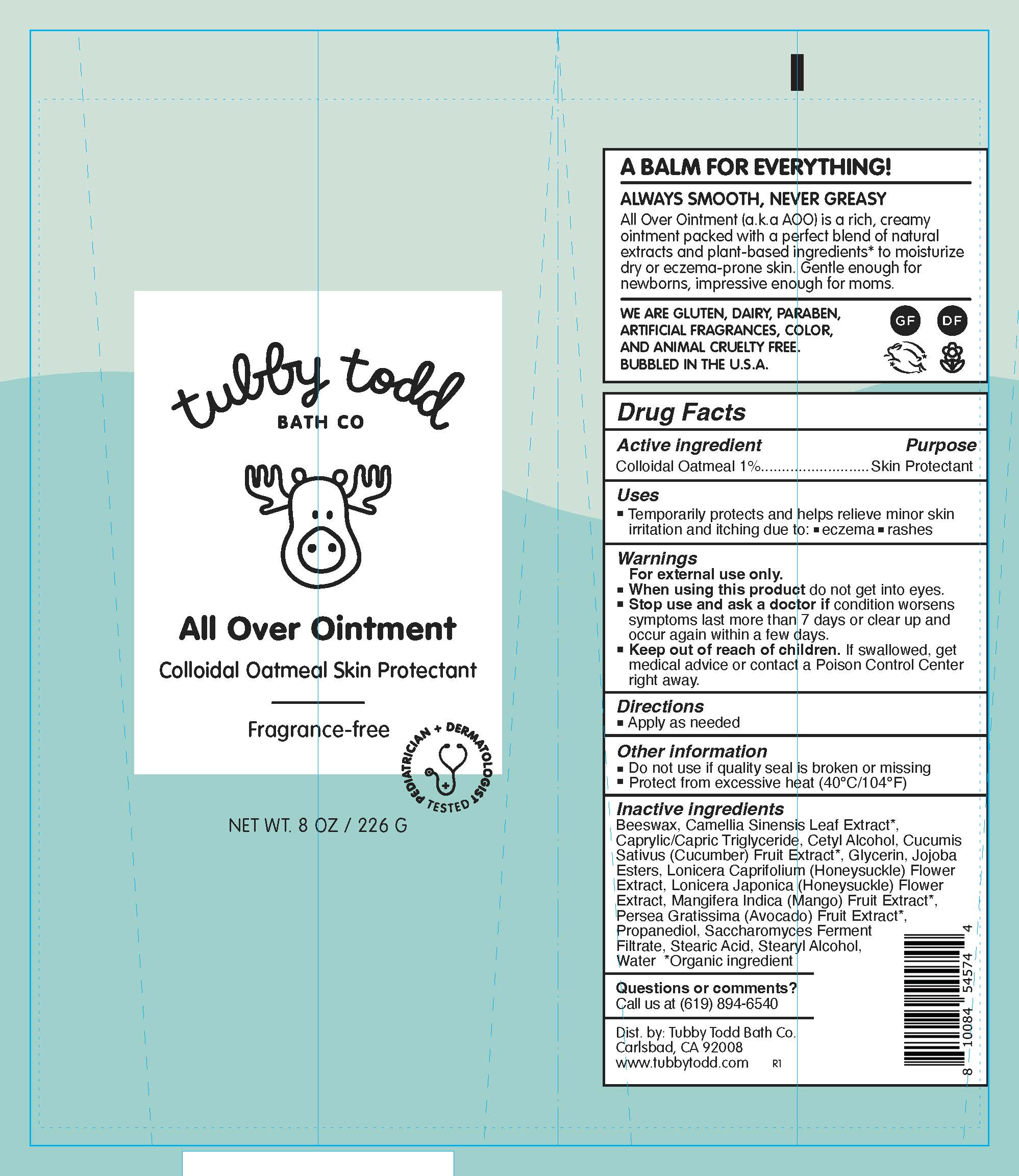 DRUG LABEL: All Over
NDC: 73088-302 | Form: OINTMENT
Manufacturer: Tubby Todd
Category: otc | Type: HUMAN OTC DRUG LABEL
Date: 20241222

ACTIVE INGREDIENTS: OATMEAL 1 g/100 g
INACTIVE INGREDIENTS: STEARYL ALCOHOL; LONICERA JAPONICA FLOWER; CAMELLIA SINENSIS LEAF; CUCUMIS SATIVUS (CUCUMBER) FRUIT; CETYL ALCOHOL; WATER; GLYCERIN; SACCHAROMYCES LYSATE; STEARIC ACID; PROPANEDIOL; CAPRYLIC/CAPRIC TRIGLYCERIDE; HYDROLYZED JOJOBA ESTERS; AVOCADO; BEESWAX; LONICERA CAPRIFOLIUM FLOWER; MANGIFERA INDICA (MANGO) FRUIT

Tubby Todd (as PLD) - All Over Ointment (73088-302)

Active Ingredients

Colloidal Oatmeal 1%

Purpose

Skin Protectant

Uses

- Temporarily protects and helps relieve minor skin irritation and itching due to:
- Eczema
- Rashes

Warnings

For External Use Only

When using this product

- do not use near eyes. In case of contact, rinse eyes thoroughly with water.

Stop use and ask a doctor if

- condition worsens.
- symptoms may last more than 7 days or clear up and occur again within a few days

Keep out of reach of children. If swollowed, seek medical advice or contact a Poison Control Center immediately.

Directions

- Apply as needed

Other Information

- Do not use if quality seal is broken or missing
- Protect from excessive heat (40°C/104°F)

Inactive ingredients

Beeswax, Camellia Sinensis Leaf Extract*, Caprylic/Capric Triglyceride, Cetyl Alcohol, Cucumis Sativus (Cucumber), Fruit Extract*, Glycerin, Jojoba Esters, Lonicera Caprifolium, (Honeysuckle) Flower Extract, Lonicera Japonica (Honeysuckle) Flower Extract, Mangifera Indica (Mango) Fruit Extract*, Persea Gratissima (Avocado) Fruit Extract*, Propanediol, Saccharomyces Ferment Filtrate, Stearic Acid, Stearyl Alcohol, Water
*Organic ingredient

Questions or comments?

Call us at (619) 894-6560